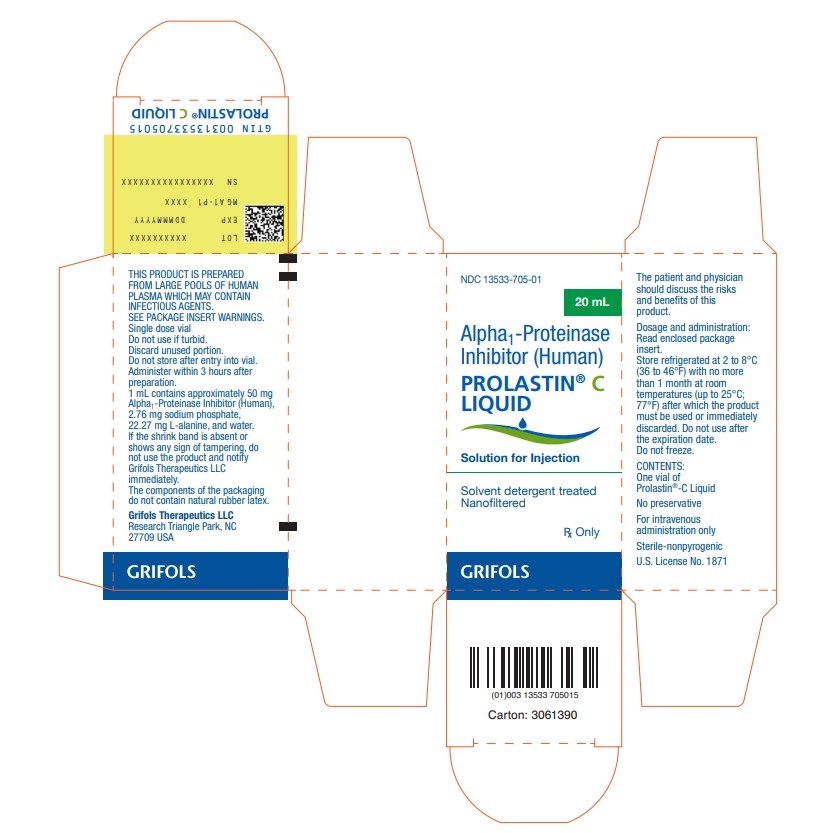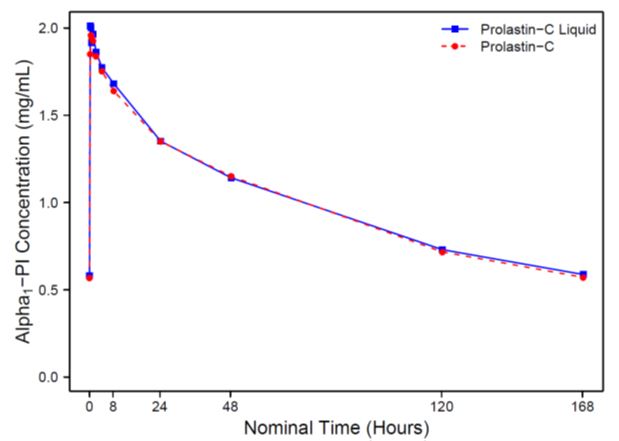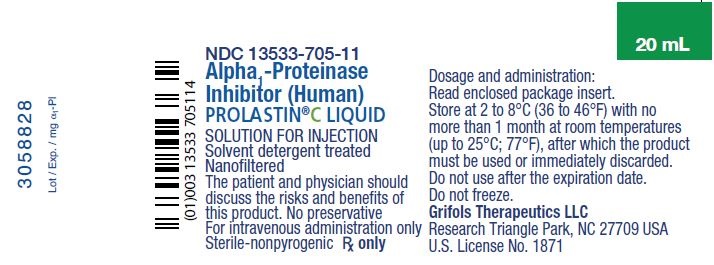 DRUG LABEL: Prolastin-C Liquid
NDC: 13533-705 | Form: INJECTION, SOLUTION
Manufacturer: GRIFOLS USA, LLC
Category: other | Type: PLASMA DERIVATIVE
Date: 20220705

ACTIVE INGREDIENTS: .alpha.1-proteinase Inhibitor Human 1000 mg/20 mL
INACTIVE INGREDIENTS: Sodium Phosphate; Alanine; Water

HIGHLIGHTS OF PRESCRIBING INFORMATION

These highlights do not include all the information needed to use PROLASTIN-C LIQUID safely and effectively. See full prescribing information for PROLASTIN-C LIQUID.
PROLASTIN-C LIQUID (Alpha1-Proteinase Inhibitor [Human])
Solution for Intravenous Injection
Initial U.S. Approval: 1987

1 INDICATIONS AND USAGE

PROLASTIN®-C LIQUID is an Alpha1-Proteinase Inhibitor (Human) (Alpha1-PI) indicated for chronic augmentation and maintenance therapy in adults with clinical evidence of emphysema due to severe hereditary deficiency of Alpha1-PI (alpha1-antitrypsin deficiency). (1)

Limitations of Use:

- The effect of augmentation therapy with any Alpha1-PI, including PROLASTIN-C LIQUID, on pulmonary exacerbations and on the progression of emphysema in Alpha1-PI deficiency has not been conclusively demonstrated in randomized, controlled clinical trials.
- Clinical data demonstrating the long-term effects of chronic augmentation or maintenance therapy with PROLASTIN-C LIQUID are not available.
- PROLASTIN-C LIQUID is not indicated as therapy for lung disease in patients in whom severe Alpha1-PI deficiency has not been established.

2 DOSAGE AND ADMINISTRATION

For intravenous use only. (2)

- Dose: 60 mg/kg body weight intravenously once per week. (2.1)
- Dose ranging studies using efficacy endpoints have not been performed with any Alpha1-PI product, including PROLASTIN-C LIQUID. (2.1)
- Administration: 0.08 mL/kg/min as determined by patient response and comfort. (2.3)

3 DOSAGE FORMS AND STRENGTHS

For injection: approximately 500 mg (10 mL), 1,000 mg (20 mL) and 4,000 mg (80 mL) of a solution for injection in single-dose vials. (3)

4 CONTRAINDICATIONS

- Immunoglobulin A (IgA) deficient patients with antibodies against IgA. (4)
- History of anaphylaxis or other severe systemic reaction to Alpha1-PI. (4)

5 WARNINGS AND PRECAUTIONS

- Severe hypersensitivity and anaphylactic reactions may occur in IgA deficient patients with antibodies against IgA. Discontinue administration of the product and initiate appropriate emergency treatment if hypersensitivity reactions occur. (5.1)
- Because PROLASTIN-C LIQUID is made from human plasma, it may carry a risk of transmitting infectious agents, e.g., viruses, the variant Creutzfeldt-Jakob disease (vCJD) agent, and, theoretically, the Creutzfeldt-Jakob disease (CJD) agent.(5.2)

6 ADVERSE REACTIONS

The most common adverse reactions during PROLASTIN-C LIQUID clinical trials in > 5% of subjects were diarrhea and fatigue, each of which occurred in 2 subjects (6%). (6.1)
To report SUSPECTED ADVERSE REACTIONS, contact Grifols Therapeutics LLC at 1-800-520-2807 or FDA at 1-800-FDA-1088 or www.fda.gov/medwatch.

FULL PRESCRIBING INFORMATION

1 INDICATIONS AND USAGE

PROLASTIN®-C LIQUID is an Alpha1-Proteinase Inhibitor (Human) (Alpha1-PI) indicated for chronic augmentation and maintenance therapy in adults with clinical evidence of emphysema due to severe hereditary deficiency of Alpha1-PI (alpha1-antitrypsin deficiency).

Limitations of Use

- The effect of augmentation therapy with any Alpha1-PI, including PROLASTIN-C LIQUID, on pulmonary exacerbations and on the progression of emphysema in Alpha1-PI deficiency has not been conclusively demonstrated in randomized, controlled clinical trials.
- Clinical data demonstrating the long-term effects of chronic augmentation or maintenance therapy with PROLASTIN-C LIQUID are not available.
- PROLASTIN-C LIQUID is not indicated as therapy for lung disease in patients in whom severe Alpha1-PI deficiency has not been established.

2 DOSAGE AND ADMINISTRATION

For intravenous use only.

2.1 Dose

- The recommended dose of PROLASTIN-C LIQUID is 60 mg/kg body weight administered intravenously once weekly.
- Dose ranging studies using efficacy endpoints have not been performed with any Alpha1-PI product.
- The carton and the label on each vial of PROLASTIN-C LIQUID show the actual amount of functionally active Alpha1-PI in milligrams (as determined by the capacity to neutralize porcine pancreatic elastase).

2.2 Preparation and Handling

1. Allow unopened PROLASTIN-C LIQUID to warm up to room temperature before administration.
2. Remove the plastic flip top from the vial.
3. Swab the exposed stopper surface with alcohol and allow to dry.
4. Inspect the PROLASTIN-C LIQUID visually for particulate matter and discoloration prior to pooling. The product may contain a few protein particles. The solution is clear, colorless or pale yellow or pale green. Do not use if the product is discolored or cloudy.
5. Pool PROLASTIN-C LIQUID from several vials to achieve the intended mg/kg body weight dose into an empty, sterile intravenous solution container using aseptic technique.
6. Keep pooled solution at room temperature for administration within three hours.
7. Discard unused portion.

2.3 Administration

- Visually inspect parenteral drug products for particulate matter and discoloration prior to administration, whenever solution and container permit. The product may contain a few protein particles. Do not use if discolored or cloudy.
- Filter the solution during administration using an intravenous administration set with a suitable 5 to 15 micron infusion filter (not supplied).
- Infuse PROLASTIN-C LIQUID separately, without mixing with other agents or diluting solutions.
- Infuse PROLASTIN-C LIQUID intravenously at 0.08 mL/kg/min as determined by patient response and comfort. The recommended dosage of 60 mg/kg takes approximately 15 minutes to infuse.

3 DOSAGE FORMS AND STRENGTHS

PROLASTIN-C LIQUID is a solution for injection containing approximately 500 mg (10 mL), 1,000 mg (20 mL), and 4,000 mg (80 mL) in single-dose vials. The actual amount of functionally active Alpha1-PI in milligrams is printed on the vial label and carton.

4 CONTRAINDICATIONS

PROLASTIN-C LIQUID is contraindicated in:

- IgA deficient patients with antibodies against IgA, due to the risk of severe hypersensitivity.
- Patients with a history of anaphylaxis or other severe systemic reaction to Alpha1-PI.

5 WARNINGS AND PRECAUTIONS

5.1 Hypersensitivity Reactions

Hypersensitivity reactions, including anaphylaxis, may occur. Monitor vital signs and observe the patient carefully throughout the infusion. Early signs and symptoms of hypersensitivity reactions may include pruritus; generalized urticaria; flushing; swollen lips, tongue, or uvula; wheezing; tightness of the chest; dyspnea; hypotension; and syncope. If hypersensitivity symptoms occur, promptly stop PROLASTIN-C LIQUID infusion and begin appropriate therapy. Have epinephrine and other appropriate therapy available for the treatment of any acute anaphylactic or anaphylactoid reaction. [see Patient Counseling Information (17)]

PROLASTIN-C LIQUID may contain trace amounts of IgA. Patients with known antibodies to IgA, which can be present in patients with selective or severe IgA deficiency, have a greater risk of developing potentially severe hypersensitivity and anaphylactic reactions.

5.2 Transmissible Infectious Agents

Because PROLASTIN-C LIQUID is made from human plasma, it may carry a risk of transmitting infectious agents, e.g., viruses, the variant Creutzfeldt-Jakob disease (vCJD) agent, and, theoretically, the Creutzfeldt-Jakob disease (CJD) agent. This also applies to unknown or emerging viruses and other pathogens. The risk of transmission of infectious agents has been reduced by screening plasma donors for prior exposure to certain infectious agents, by testing for the presence of certain virus infections, and by including steps in the manufacturing process with the demonstrated capacity to inactivate and /or remove certain infectious agents. Despite these measures, this product may still potentially transmit disease.

Report all infections thought by a physician possibly to have been transmitted by this product to Grifols Therapeutics LLC (1-800-520-2807).

6 ADVERSE REACTIONS

The most serious adverse reaction observed during clinical trials with PROLASTIN-C was an abdominal and extremity rash in one subject. [see Warnings and Precautions (5.1)]

The most common adverse reactions observed at a rate of > 5% in subjects receiving PROLASTIN-C LIQUID were diarrhea and fatigue, each of which occurred at a rate of 6% (two subjects each).

6.1 Clinical Trials Experience

Because clinical studies are conducted under widely varying conditions, adverse reaction rates observed cannot be directly compared to rates in other clinical trials and may not reflect the rates observed in practice.

One clinical trial was conducted with PROLASTIN-C LIQUID: a 16 week, multicenter, randomized, double-blind crossover study to assess the safety, immunogenicity, and pharmacokinetic comparability of PROLASTIN-C LIQUID to PROLASTIN-C in 32 subjects.

Adverse reactions (as defined in the footnote to Table 1) occurring in >5% of subjects during the 16 week double-blind crossover treatment period are shown in Table 1.

Table 1: Adverse Reactions Occurring in >5% of Subjects during the Double-Blinded Crossover Treatment
 | PROLASTIN®-C LIQUID (N=32) | PROLASTIN®-C (N=31)
Adverse Reaction [An adverse reaction is defined as any adverse event that occurred where either a) the event was not considered “unrelated” to administration of the product, or b) the occurrence was during or within 72 hours of the end of the previous infusion of the product, or c) the investigator's causality assessment of the event was missing or indeterminate, or d) the incidence during treatment with 1 investigational product was 130% or more of the incidence during treatment with the other investigational product.] , [Source: the randomized double-blinded comparator trial of PROLASTIN-C LIQUID vs PROLASTIN-C.] | No. of Subjects with Adverse Reaction (percentage of all subjects) | No. of Subjects with Adverse Reaction (percentage of all subjects)
Diarrhea | 2 (6) | 0
Fatigue | 2 (6) | 0

Table 2 below displays the adverse reaction (defined as per Table 1) rate as a percentage of infusions received during the 16 week double-blinded treatment period.

Table 2: Adverse Reaction Frequency as a Percent of All Infusions and Occurring More than Once in the PROLASTIN®-C LIQUID Group during the 16 Week Double Blinded Treatment Period
 | PROLASTIN®-C LIQUID No. of infusions: 252 | PROLASTIN®-C No. of infusions: 245
Adverse Reaction [Source: the randomized double-blinded comparator trial of PROLASTIN-C LIQUID vs PROLASTIN-C.] | No. of Adverse Reactions (percentage of all infusions) | No. of Adverse Reactions (percentage of all infusions)
Diarrhea | 3 (1.2) | 0
Fatigue | 2 (0.8) | 0

A total of 23 COPD exacerbations were reported for a total of 18 individual subjects. Twelve subjects (12/32, 38%) during PROLASTIN-C LIQUID treatment experienced 13 COPD exacerbations, and 9 subjects (9/31, 29%) during PROLASTIN-C treatment had 10 COPD exacerbations. Three COPD exacerbations occurred during the Follow-Up Period after PROLASTIN-C LIQUID treatment and 1 COPD exacerbation occurred in the Follow-up period after PROLASTIN-C treatment. The overall rate of pulmonary exacerbations during treatment with either product was 1.9 exacerbations per subject-year. No exacerbation was considered to be serious, except for one event after PROLASTIN-C treatment during the Follow-Up period (due to hospitalization).

Two separate prior clinical trials were conducted with PROLASTIN-C: 1.) a 20 week, open-label, single arm safety study in 38 subjects (single-arm open-label trial), and 2.) a 16 week, randomized, double-blind, crossover pharmacokinetic comparability study vs. PROLASTIN in 24 subjects, followed by an 8 week open-label treatment with PROLASTIN-C (randomized double-blinded comparator trial). Thus, a total of 93 subjects were exposed to PROLASTIN-C in clinical trials.

The most serious adverse reaction observed during clinical trials with PROLASTIN-C was an abdominal and extremity rash in one subject. The rash resolved subsequent to outpatient treatment with antihistamines and steroids. Two instances of a less severe, pruritic abdominal rash were observed upon rechallenge despite continued antihistamine and steroid treatment, which led to withdrawal of the subject from the trial.

Grifols assessed the randomized double-blinded comparator trial of PROLASTIN and PROLASTIN-C for adverse reactions (as defined in the footnote to Table 3) occurring during each 8 week double-blind crossover treatment period, as shown in Table 3.

Table 3: Adverse Reactions Occurring during the First 8 Weeks of Each Double-Blinded Treatment
 | PROLASTIN®-C No. of subjects: 24 | PROLASTIN® No. of subjects: 24
Adverse Reaction [An adverse reaction is defined as any adverse event where either a) the incidence with PROLASTIN-C was greater than with PROLASTIN, or b) the occurrence was within 72 hours of treatment, or c) the event was otherwise considered related or possibly related to the drug.] , [Source: the randomized double-blinded comparator trial.] | No. of Subjects with Adverse Reaction (percentage of all subjects) | No. of Subjects with Adverse Reaction (percentage of all subjects)
Upper respiratory tract infection | 3 (12.5%) | 1 (4.2%)
Headache | 1 (4.2%) | 2 (8.3%)
Pruritus | 1 (4.2%) | 0
Urticaria | 1 (4.2%) | 0
Nausea | 1 (4.2%) | 0
Peripheral edema | 1 (4.2%) | 0
Pyrexia | 1 (4.2%) | 0

Table 4 below displays the adverse reaction (defined as per Table 3) rate as a percentage of infusions received during the 8 weeks of each double-blinded treatment.

Table 4: Adverse Reaction Frequency as a Percent of All Infusions during the First 8 Weeks of Each Double-Blinded Infusion Treatment
 | PROLASTIN®-C No. of infusions: 188 | PROLASTIN® No. of infusions: 192
Adverse Reaction [Source: the randomized double-blinded comparator trial.] | No. of Adverse Reactions (percentage of all infusions) | No. of Adverse Reactions (percentage of all infusions)
Upper respiratory tract infection | 3 (1.6%) | 1 (0.5%)
Headache | 1 (0.5%) | 3 (1.6%)
Pruritus | 1 (0.5%) | 0
Urticaria | 1 (0.5%) | 0
Nausea | 1 (0.5%) | 0
Peripheral edema | 1 (0.5%) | 0
Pyrexia | 1 (0.5%) | 0

Table 5 below displays the adverse reactions occurring in two or more subjects during the single-arm open-label trial.

Table 5: Adverse Reactions Occurring in Two or More Subjects (>5%) during the 20 Week Single-Arm Open-Label Trial
 | PROLASTIN®-C No. of subjects: 38
Adverse Reaction [An adverse reaction is defined as any adverse event that occurred where either a) the occurrence was within 72 hours of treatment, or b) the event was otherwise considered related or possibly related to the drug.] , [Source: the single-arm, open-label trial.] | No. of Subjects with Adverse Reaction (percentage of all subjects)
Upper respiratory tract infection | 6 (15.8%)
Urinary tract infection | 5 (13.2%)
Nausea | 4 (10.5%)
Chest pain | 3 (7.9%)
Back pain | 2 (5.3%)
Chills | 2 (5.3%)
Cough | 2 (5.3%)
Dizziness | 2 (5.3%)
Dyspnea | 2 (5.3%)
Headache | 2 (5.3%)
Hot flush | 2 (5.3%)
Oral candidiasis | 2 (5.3%)

Ten exacerbations of chronic obstructive pulmonary disease were reported by 8 subjects in the 24 week crossover pharmacokinetic study. During the 16 week double-blind crossover phase, 4 subjects (17%) had a total of 4 exacerbations during PROLASTIN-C treatment and 4 subjects (17%) had a total of 4 exacerbations during PROLASTIN treatment. Two additional exacerbations in 2 subjects (8%) occurred during the 8 week open-label treatment period with PROLASTIN-C. The overall rate of pulmonary exacerbations during treatment with either product was 0.9 exacerbations per subject-year.

Immunogenicity

The detection of antibody formation is highly dependent on the sensitivity and specificity of the assay. Additionally, the observed incidence of antibody (including neutralizing antibody) positivity in an assay may be influenced by several factors including assay methodology, sample handling, timing of sample collection, concomitant medications, and underlying disease. For these reasons, comparison of the incidence of antibodies to PROLASTIN-C LIQUID with the incidence of antibodies to other products may be misleading.

In the randomized, crossover pharmacokinetic clinical trial, no immunogenicity response was observed in subjects dosed with PROLASTIN-C LIQUID or PROLASTIN-C.

In the single-arm, open-label safety clinical trial, three treatment naïve subjects out of 36 subjects evaluated developed antibody to Alpha1-PI at week 24 after receiving PROLASTIN-C. A fourth subject (non-naïve) was positive prior to and after receiving PROLASTIN-C, but levels were unchanged during the study. None of the four antibody specimens was able to neutralize the protease inhibitor capacity of PROLASTIN-C. In the randomized, crossover pharmacokinetic clinical trial comparing PROLASTIN-C and PROLASTIN, none of 24 subjects developed antibodies to PROLASTIN-C.

6.2 Postmarketing Experience

Because postmarketing reporting of adverse reactions is voluntary and from a population of uncertain size, it is not always possible to reliably estimate the frequency of these reactions or establish a causal relationship to product exposure.

Expected postmarketing experience for PROLASTIN-C LIQUID is based on the reactions reported for PROLASTIN-C. The reactions which have been chosen for inclusion due to their seriousness, frequency of reporting, possible causal connection to PROLASTIN®-C, or a combination of these factors, are:

- General/Body as a Whole: Fatigue, malaise, influenza-like illness, pain, asthenia
- Immune system: Hypersensitivity including anaphylactoid/anaphylactic reactions
- Cardiovascular: Tachycardia
- Musculoskeletal: Arthralgia, myalgia
- Gastrointestinal: Vomiting, diarrhea
- Investigation: Blood pressure increased

8 USE IN SPECIFIC POPULATIONS

8.1 Pregnancy

Risk Summary

There are no data with PROLASTIN-C LIQUID use in pregnant women to inform a drug-associated risk. Animal reproduction studies have not been conducted with PROLASTIN-C LIQUID. It is not known whether PROLASTIN-C LIQUID can cause fetal harm when administered to a pregnant woman or can affect reproduction capacity. PROLASTIN-C LIQUID should be given to a pregnant woman only if clearly needed.

In the U.S. general population, the estimated background risk of major birth defect and miscarriage in clinically recognized pregnancies is 2-4% and 15-20%, respectively.

8.2 Lactation

Risk Summary

There is no information regarding the presence of PROLASTIN-C LIQUID in human milk, the effects on the breastfed infant, or the effects on milk production. The developmental and health benefits of breastfeeding should be considered along with the mother’s clinical need for PROLASTIN-C LIQUID and any potential adverse effects on the breastfed infant from PROLASTIN-C LIQUID or from the underlying maternal condition.

8.4 Pediatric Use

Safety and effectiveness in the pediatric population have not been established.

8.5 Geriatric Use

Clinical studies of PROLASTIN-C LIQUID did not include sufficient numbers of subjects aged 65 and over to determine whether they respond differently from younger subjects. As for all patients, dosing for geriatric patients should be appropriate to their overall situation.

11 DESCRIPTION

PROLASTIN-C LIQUID is a sterile, concentrate of Alpha1-PI for intravenous infusion. The solution is clear, colorless or pale yellow or pale green. The actual amount of functionally active Alpha1-PI in milligrams, as determined by capacity to neutralize porcine pancreatic elastase, is printed on the carton and vial label of PROLASTIN-C LIQUID. The specific activity of PROLASTIN-C LIQUID is ≥ 0.7 mg functional Alpha1-PI per mg of total protein. PROLASTIN-C LIQUID has a purity of ≥ 90% Alpha1-PI (Alpha1-PI protein/total protein). PROLASTIN-C LIQUID has a pH of 6.6–7.4, a sodium phosphate content of 0.013–0.025 M, and is stabilized with 0.20-0.30 M of alanine. The total sodium concentration is ≤ 100 mEq/L. PROLASTIN-C LIQUID contains no preservative.

PROLASTIN-C LIQUID is produced from pooled human plasma through modifications of the PROLASTIN process using purification by polyethylene glycol (PEG) precipitation, anion exchange chromatography, and cation exchange chromatography. All Source Plasma used in the manufacture of PROLASTIN-C LIQUID is non-reactive (negative) by FDA-licensed serological test methods for hepatitis B surface antigen (HBsAg) and antibodies to hepatitis C virus (HCV) and human immunodeficiency virus types 1 and 2 and negative by FDA-licensed Nucleic Acid Technologies (NAT) for HCV and human immunodeficiency virus type 1 (HIV-1). In addition, all Source Plasma is negative for hepatitis B virus (HBV) by either an FDA-licensed or investigational NAT assay. The goal of the investigational HBV NAT test is to detect low levels of viral nucleic acid; however, the significance of a negative result for the investigational HBV NAT test has not been established. By in-process NAT, all Source Plasma is negative for hepatitis A virus (HAV). As a final plasma safety step, all plasma manufacturing pools are tested by serological test methods and NAT.

To evaluate further the virus safety profile of PROLASTIN-C LIQUID, in vitro studies have been conducted to validate the capacity of the manufacturing process to reduce the infectious titer of a wide range of viruses with diverse physicochemical properties. These studies evaluated the inactivation/removal of clinically relevant viruses, including human immunodeficiency virus type 1 (HIV-1) and hepatitis A virus (HAV), as well as the following model viruses: bovine viral diarrhea virus (BVDV), a surrogate for hepatitis C virus; pseudorabies virus (PRV), a surrogate for large enveloped DNA viruses (e.g., herpes viruses); vesicular stomatitis virus (VSV), a model for enveloped viruses; reovirus type 3 (Reo3), a non-specific model for non-enveloped viruses; and porcine parvovirus (PPV), a model for human parvovirus B19.

The PROLASTIN-C LIQUID manufacturing process has several steps (Cold Ethanol Fractionation, PEG Precipitation, and Depth Filtration) that are important for purifying Alpha1-PI as well as removing potential virus contaminants. Two additional steps, Solvent/Detergent Treatment and 15 nm Virus Removal Nanofiltration, are included in the process as dedicated pathogen reduction steps. The Solvent/Detergent Treatment step effectively inactivates enveloped viruses (such as HIV-1, VSV, HBV, and HCV). The 15 nm Virus Removal Nanofiltration step has been implemented to reduce the risk of transmission of enveloped and non-enveloped viruses as small as 18 nm. Table 6 presents the virus reduction capacity of each process step and the accumulated virus reduction for the process as determined in viral validation studies in which virus was deliberately added to a process model in order to study virus reduction. In addition, the Solvent/Detergent Treatment step inactivates ≥ 5.4 log10 of West Nile virus, a clinically relevant enveloped virus.

Table 6: Virus Reduction (Log10) for the PROLASTIN®-C LIQUID Manufacturing Process
Process Step | Enveloped Viruses |  |  |  | Non-enveloped Viruses
Process Step | HIV-1 | BVDV | PRV | VSV | Reo3 | HAV | PPV
Cold Ethanol Fractionation | 1.5 | 1.7 | 2.5 | ND [Not determined. VSV inactivation and/or removal was only determined for the Solvent/Detergent Treatment and 15 nm Virus Removal Nanofiltration steps.] | ≥ 2.1 | 1.4 | 1.0
PEG Precipitation | 4.3 | 2.8 | 3.3 | ND | 3.3 | 3.0 | 3.2
Depth Filtration | ≥ 4.7 | 4.0 | ≥ 4.8 | ND | ≥ 4.0 | ≥ 2.8 | ≥ 4.4
Solvent/Detergent Treatment | ≥ 6.2 | ≥ 4.6 | ≥ 4.3 | 5.1 | NA [Not applicable. This step is only effective against enveloped viruses.] | NA | NA
15 nm Virus Removal Nanofiltration | ≥ 6.9 | ≥ 4.7 | ≥ 5.2 | ≥ 5.1 | ≥ 4.3 | ≥ 5.5 | 4.2
Accumulated Virus Reduction | ≥ 23.6 | ≥ 17.8 | ≥ 20.1 | ≥ 10.2 | ≥ 13.7 | ≥ 12.7 | ≥ 12.8

Additionally, the manufacturing process was investigated for its capacity to decrease the infectivity of an experimental agent of transmissible spongiform encephalopathy (TSE), considered as a model for the variant Creutzfeldt-Jakob disease (vCJD) and Creutzfeldt-Jakob disease (CJD) agents. Studies of the PROLASTIN-C LIQUID manufacturing process demonstrate that a minimum of 6 log10 reduction of TSE infectivity is achieved. These studies provide reasonable assurance that low levels of vCJD/CJD agent infectivity, if present in the starting material, would be removed.

12 CLINICAL PHARMACOLOGY

12.1 Mechanism of Action

Alpha1-PI deficiency is an autosomal, co-dominant, hereditary disorder characterized by low serum and lung levels of Alpha1-PI. Smoking is an important risk factor for the development of emphysema in patients with Alpha1-PI deficiency.(1,2) Because emphysema affects many, but not all individuals with the more severe genetic variants of Alpha1-PI deficiency, augmentation therapy with Alpha1-PI is indicated only in patients with severe Alpha1-PI deficiency who have clinically evident emphysema.

Only some Alpha1-PI alleles are associated with clinically apparent Alpha1-PI deficiency.(3,4) Approximately 95% of all severely deficient patients are homozygous for the PiZ allele.(4) Individuals with the PiZZ variant typically have serum Alpha1-PI levels less than 35% of the average normal level. Individuals with the Pi(null)(null) variant have undetectable Alpha1-PI protein in their serum. Individuals with these low serum Alpha1-PI levels, i.e., less than 11 µM, have a markedly increased risk for developing emphysema over their lifetimes. In addition, PiSZ individuals, whose serum Alpha1-PI levels range from approximately 9 to 23 µM,(5) are considered to have moderately increased risk for developing emphysema, regardless of whether their serum Alpha1-PI levels are above or below 11 µM.

Augmenting the levels of functional protease inhibitor by intravenous infusion is an approach to therapy for patients with Alpha1-PI deficiency. The intended theoretical goal is to provide protection to the lower respiratory tract by correcting the imbalance between neutrophil elastase and protease inhibitors. Whether augmentation therapy with any Alpha1-PI product actually protects the lower respiratory tract from progressive emphysematous changes has not been demonstrated in adequately powered, randomized controlled, clinical trials. Although the maintenance of blood serum levels of Alpha1-PI (antigenically measured) above 11 µM has been historically postulated to provide therapeutically relevant anti-neutrophil elastase protection,(6) this has not been proven. Individuals with severe Alpha1-PI deficiency have been shown to have increased neutrophil and neutrophil elastase concentrations in lung epithelial lining fluid compared to normal PiMM individuals, and some PiSZ individuals with Alpha1-PI above 11 µM have emphysema attributed to Alpha1-PI deficiency. These observations underscore the uncertainty regarding the appropriate therapeutic target serum level of Alpha1-PI during augmentation therapy.

The pathogenesis of emphysema is understood as described in the “protease-antiprotease imbalance” model. Alpha1-PI is understood to be the primary antiprotease in the lower respiratory tract, where it inhibits neutrophil elastase (NE). Normal healthy individuals produce sufficient Alpha1-PI to control the NE produced by activated neutrophils and are thus able to prevent inappropriate proteolysis of the lung tissue by NE. Conditions that increase neutrophil accumulation and activation in the lung, such as respiratory infection and smoking, will in turn increase levels of NE. However, individuals who are severely deficient in endogenous Alpha1-PI are unable to maintain an appropriate antiprotease defense, and, in addition, they have been shown to have increased lung epithelial lining fluid neutrophil and NE concentrations. Because of these factors, many (but not all) individuals who are severely deficient in endogenous Alpha1-PI are subject to more rapid proteolysis of the alveolar walls leading to chronic lung disease. PROLASTIN-C LIQUID serves as Alpha1-PI augmentation therapy in the patient population with severe Alpha1-PI deficiency and emphysema, acting to increase and maintain serum and lung epithelial lining fluid levels of Alpha1-PI.

12.2 Pharmacodynamics

Chronic augmentation therapy with the predecessor product, PROLASTIN®, administered weekly at a dose of 60 mg/kg body weight, results in increased levels of Alpha1-PI and functional anti-neutrophil elastase capacity in the epithelial lining fluid of the lower respiratory tract of the lung, as compared to levels prior to commencing therapy with PROLASTIN.(7) However, the clinical benefit of the increased levels at the recommended dose has not been demonstrated in adequately powered, randomized, controlled clinical trials for any Alpha1-PI product.

PROLASTIN-C LIQUID increases antigenic and functional (anti-neutrophil elastase capacity, ANEC) serum levels.

12.3 Pharmacokinetics

The pharmacokinetic (PK) study was a randomized, double-blind, crossover trial comparing PROLASTIN-C LIQUID to PROLASTIN-C (Alpha1-Proteinase Inhibitor [Human]) conducted in 32 adult subjects age 44 to 71 years with severe Alpha1-PI deficiency. Eighteen subjects were male and 14 subjects were female. Sixteen subjects were randomized to each treatment sequence. All but one subject had the PiZZ genotype and the remaining subject was PiSZ. Twenty-eight subjects had received prior Alpha1-PI augmentation therapy and 4 subjects were naïve to Alpha1-PI augmentation therapy. Study subjects were randomly assigned to receive either 60 mg/kg body weight of functional PROLASTIN-C LIQUID or PROLASTIN-C weekly by intravenous infusion during the first 8-week treatment period. Following the last dose in the first 8-week treatment period, subjects underwent serial blood sampling for PK analysis and then crossed over to the alternate treatment for the second 8-week treatment period. Following the last treatment in the second 8-week treatment period, subjects underwent serial blood sampling for PK analysis. In addition, blood samples were drawn for trough levels before infusion at Weeks 6, 7, 8, and 9, as well as before infusion at Weeks 14, 15, 16, and 17. A final PK sample was drawn at Week 20 (4 weeks after the last dose) to correct for endogenous Alpha1-PI levels.

The key pharmacokinetic parameter was the area under the serum Alpha1-PI concentration-by-antigenic-assay-time curve (AUC0-7days) following 8 weeks of treatment with PROLASTIN-C LIQUID or PROLASTIN-C. The 90% confidence interval (1.03-1.08) for the ratio of AUC0-7days for PROLASTIN-C LIQUID and PROLASTIN-C indicated that the 2 products are bioequivalent, i.e. the entire range falls within the 0.80 – 1.25 interval. AUC0-7days of the serum-equivalent Alpha1-PI concentration by functional assay and Cmax by antigenic and functional assays gave comparable results for PROLASTIN-C LIQUID and PROLASTIN-C, as shown in Table 7.

Table 7: Results of Statistical Analysis of Pharmacokinetic Parameters at Steady-State (PK Population)
Treatment | AUC0-7days (mg*h/mL)
Treatment | Antigenic Content |  |  | Functional Activity
Treatment | Geometric LSM | Geometric LSM Ratio | 90% CI of Geometric LSM Ratio | Geometric LSM | Geometric LSM Ratio | 90% CI of Geometric LSM Ratio
PROLASTIN®-C LIQUID n=30 | 203.57 | 1.05 | 1.03, 1.08 | 169.86 | 1.04 | 1.01, 1.07
PROLASTIN®-C n=28 | 193.71 | 1.05 | 1.03, 1.08 | 163.52 | 1.04 | 1.01, 1.07
Treatment | Cmax (mg/mL)
PROLASTIN®-C LIQUID n=30 | 2.517 | 1.04 | 1.00, 1.09 | 2.062 | 1.04 | 1.00, 1.07
PROLASTIN®-C n=28 | 2.415 | 1.04 | 1.00, 1.09 | 1.992 | 1.04 | 1.00, 1.07

The half life (t1/2) for antigenic content was comparable, specifically 156.39 hours versus 164.10 hours for PROLASTIN-C LIQUID versus PROLASTIN-C, respectively. Similar half life was also observed when assessed by functional activity between PROLASTIN-C LIQUID versus PROLASTIN-C (126.57 hours versus 126.82 hours respectively).

Figure 1 shows the serum-equivalent concentration (functional activity) vs. time curves of Alpha1-PI after intravenous administration of PROLASTIN-C LIQUID and PROLASTIN-C.

Figure 1: Mean Serum-equivalent Alpha1-PI Concentration (functional activity) vs. Time Curves Following Treatment with PROLASTIN®-C LIQUID or PROLASTIN®-C

Serum trough levels measured at steady state during the PK study using an antigenic content assay showed PROLASTIN-C LIQUID resulted in a mean trough of 17.7 µM and PROLASTIN-C resulted in a mean trough of 16.9 µM.

A randomized, double-blind, crossover pharmacokinetic (PK) study comparing PROLASTIN-C to PROLASTIN was conducted in 24 adult subjects age 40 to 72 with severe Alpha1-PI deficiency. Ten subjects were male and 14 subjects were female. All but one subject had the PiZZ genotype and the remaining subject had PiSZ. All subjects had received prior Alpha1-PI therapy with PROLASTIN for at least 1 month. The double-blind portion of the study was designed the same as the randomized, double-blind, crossover PK study comparing PROLASTIN-C LQUID to PROLASTIN-C described above.

The pharmacokinetic parameters of Alpha1-PI in plasma, based on serum-equivalent functional activity assays, showed comparability between PROLASTIN-C treatment and PROLASTIN treatment, as shown in Table 8.

Table 8: Pharmacokinetic Parameters of Alpha1-PI in Plasma
Treatment | AUC0-7 days (hr*mg/mL) Mean (%CV) | Cmax (mg/mL) Mean (%CV) | t1/2 (hr) Mean (%CV)
PROLASTIN®-C (n=22 or 23) | 155.9 (17%) | 1.797 (10%) | 146.3 (16%)
PROLASTIN® (n=22 or 23) | 152.4 (16%) | 1.848 (15%) | 139.3 (18%)

The key pharmacokinetic parameter was the area under the plasma Alpha1-PI concentration-by-antigenic-assay-time curve (AUC0-7days) following 8 weeks of treatment with PROLASTIN-C or PROLASTIN. The 90% confidence interval (0.97-1.09) for the ratio of AUC0-7days for PROLASTIN-C and PROLASTIN indicated that the 2 products are bioequivalent, i.e. the entire range falls within the 0.80 – 1.25 interval.

Serum-equivalent trough levels measured during the crossover PK study via an antigenic content assay showed PROLASTIN-C treatment resulted in a mean trough of 16.9 ± 2.3 µM and PROLASTIN resulted in a mean trough of 16.7 ± 2.7 µM. Using the functional activity assay, PROLASTIN-C resulted in a mean trough of 11.8 ± 2.2 µM and PROLASTIN resulted in a mean trough of 11.0 ± 2.2 µM.

13 NONCLINICAL TOXICOLOGY

13.1 Carcinogenesis, Mutagenesis, Impairment of Fertility

Carcinogenesis, mutagenesis, and impairment of fertility studies were not performed; PROLASTIN-C LIQUID is a biologic purified from human plasma.

13.2 Animal Toxicology and/or Pharmacology

Intravenous administration of five daily doses of PROLASTIN-C LIQUID to rabbits at a dose up to 600 mg/kg per day (10-fold higher dose than the recommended human dose of 60 mg/kg administered weekly), did not result in any signs of toxicity. Further, there were no differences in safety and tolerability of PROLASTIN-C and PROLASTIN-C LIQUID in nonclinical testing.

14 CLINICAL STUDIES

The clinical efficacy of PROLASTIN-C LIQUID in influencing the course of pulmonary emphysema or pulmonary exacerbations has not been demonstrated in adequately powered, randomized, controlled clinical trials.

A total of 23 subjects with the PiZZ variant and documented emphysema were studied in a single-arm, open label clinical trial with PROLASTIN, the predecessor product. Nineteen of the subjects received PROLASTIN, 60 mg/kg, once weekly for up to 26 weeks (average 24 weeks). Blood levels of Alpha1-PI were maintained above 11 µM. Bronchoalveolar lavage studies demonstrated statistically significant increased levels of Alpha1-PI and functional ANEC in the epithelial lining fluid of the lower respiratory tract of the lung, as compared to levels prior to dosing.

In addition to the PROLASTIN-C LIQUID/PROLASTIN-C crossover trial described above, in which 31 subjects received PROLASTIN-C, PROLASTIN-C has been studied in 62 individual subjects in 2 separate clinical trials. The first study was a crossover pharmacokinetic study. [see Clinical Pharmacology (12.3)] The second PROLASTIN-C clinical trial was a multi-center, open-label single arm safety study conducted to evaluate the safety and tolerability of PROLASTIN-C. In this study, 38 subjects were treated with weekly intravenous infusions of 60 mg/kg body weight of PROLASTIN-C for 20 weeks. Half the subjects were naïve to previous Alpha1-PI augmentation prior to study entry and the other half were receiving augmentation with PROLASTIN prior to entering the study. A diagnosis of severe Alpha1-PI deficiency was confirmed by the demonstration of the PiZZ genotype in 32 of 38 (84.2%) subjects, and 6 of 38 (15.8%) subjects presented with other alleles known to result in severe Alpha1-PI deficiency. These groups were distributed evenly between the naïve and non-naïve cohorts.

15 REFERENCES

1. American Thoracic Society; European Respiratory Society. American Thoracic Society/European Respiratory Society statement: standards for the diagnosis and management of individuals with alpha-1 antitrypsin deficiency. Am J Respir Crit Care Med. 2003;168:818-900.
2. Molloy K, Hersh CP, Morris VB, et al. Clarification of the risk of chronic obstructive pulmonary disease in α1-antitrypsin deficiency PiMZ heterozygotes. Am J Respir Crit Care Med. 2014;7:419-27.
3. Crystal RG. α1-Antitrypsin deficiency, emphysema, and liver disease; genetic basis and strategies for therapy. J Clin Invest. 1990;85:1343-52.
4. World Health Organization. Alpha-1-antitrypsin deficiency: Memorandum from a WHO meeting. Bull World Health Organ. 1997;75:397-415.
5. Turino GM, Barker AF, Brantly ML, Cohen AB, Connelly RP, Crystal RG, et al. Clinical features of individuals with PI*SZ phenotype of α1-antitrypsin deficiency. Am J Respir Crit Care Med. 1996;154:1718-25.
6. American Thoracic Society. Guidelines for the approach to the patient with severe hereditary alpha-1-antitrypsin deficiency. Am Rev Respir Dis. 1989;140:1494-7.
7. Wewers MD, Casolaro MA, Sellers SE, Swayze SC, McPhaul KM, Wittes JT, et al. Replacement therapy for alpha1-antitrypsin deficiency associated with emphysema. N Eng J Med. 1987;316:1055-62.

16 HOW SUPPLIED/STORAGE AND HANDLING

- PROLASTIN-C LIQUID is supplied in single-dose vials with the total Alpha1-PI functional activity, in milligrams, stated on the vial label and carton.
- Components of the packaging do not contain natural rubber latex.

Carton NDC | Vial NDC | Approximate Alpha1–PI Functional Activity | Volume
13533-705-31 13533-705-01 13533-705-51 | 13533-705-32 13533-705-11 13533-705-52 | 500 mg 1,000 mg 4,000 mg | 10 mL 20 mL 80 mL

- Store refrigerated at 2-8°C (36-46°F) for the period indicated by the expiration date on its label.
  - Product may be stored at room temperatures not exceeding 25oC (77oF) for up to one month, after which the product must be used or immediately discarded.
- Do not freeze.
- Discard unused portion.

17 PATIENT COUNSELING INFORMATION

- Inform patients of the signs of hypersensitivity reactions including pruritus; generalized urticaria; flushing; swollen lips, tongue, or uvula; wheezing; tightness of the chest; dyspnea; hypotension; and syncope. Advise patients to discontinue use of the product and contact their physician and/or seek immediate emergency care, depending on the severity of the reaction, if these symptoms occur. [see Warnings and Precautions (5.1)]
- Inform patients that PROLASTIN-C LIQUID is made from human plasma and may carry a risk of transmitting infectious agents that can cause disease (e.g., viruses, the vCJD agent and, theoretically, the CJD agent). Explain that the risk of PROLASTIN-C LIQUID transmitting an infectious agent has been reduced by screening plasma donors for prior exposure to certain infectious agents, by testing the donated plasma for certain current virus infections, and by inactivating and/or removing infectious agents during manufacturing. [see Warnings and Precautions (5.2)]
- Inform patients that administration of PROLASTIN-C LIQUID has been demonstrated to raise the plasma level of Alpha1-PI, but that the effect of this augmentation on pulmonary exacerbations and on the rate of progression of emphysema has not been demonstrated in adequately powered, randomized, controlled clinical trials for any Alpha1-PI product. [see Clinical Studies (14)]

Manufactured by:
Grifols Therapeutics LLC
Research Triangle Park, NC 27709 USA
U.S. License No. 1871
3062338 / 3062339

PACKAGE LABEL

NDC 13533-705-01
20 mL
Alpha1-Proteinase Inhibitor (Human)
PROLASTIN® C
LIQUID
Solution for Injection
Solvent detergent treated
Nanofiltered
Rx Only
GRIFOLS
The patient and physician
should discuss the risks
and benefits of this
product.
Dosage and administration:
Read enclosed package
insert.
Store refrigerated at 2 to 8°C
(36 to 46°F) with no more
than 1 month at room
temperatures (up to 25°C;
77°F) after which the product
must be used or immediately
discarded. Do not use after
the expiration date.
Do not freeze.
CONTENTS:
One vial of
Prolastin®-C Liquid
No preservative
For intravenous
administration only
Sterile-nonpyrogenic
U.S. License No. 1871
THIS PRODUCT IS PREPARED
FROM LARGE POOLS OF HUMAN
PLASMA WHICH MAY CONTAIN
INFECTIOUS AGENTS.
SEE PACKAGE INSERT WARNINGS.
Single dose vial
Do not use if turbid.
Discard unused portion.
Do not store after entry into vial.
Administer within 3 hours after
preparation.
1 mL contains approximately 50 mg
Alpha1-Proteinase Inhibitor (Human),
2.76 mg sodium phosphate,
22.27 mg L-alanine, and water.
If the shrink band is absent or
shows any sign of tampering, do
not use the product and notify
Grifols Therapeutics LLC
immediately.
The components of the packaging
do not contain natural rubber latex.
Grifols Therapeutics LLC
Research Triangle Park, NC
27709 USA
GRIFOLS
Carton: 3061390
LOT XXXXXXXXXX
EXP DDMMMYYYY
MG A1-P1 XXXX
SN XXXXXXXXXXXXXXXX
GTIN 00313533705015
PROLASTIN® C LIQUID

NDC 13533-705-11
Alpha1-Proteinase
Inhibitor (Human)
PROLASTIN® C LIQUID
SOLUTION FOR INJECTION
Solvent detergent treated
Nanofiltered
The patient and physician should
discuss the risks and benefits of
this product. No preservative
For intravenous administration only
Sterile-nonpyrogenic
Rx only
20 mL
Dosage and administration:
Read enclosed package insert.
Store at 2 to 8°C (36 to 46°F) with no
more than 1 month at room temperatures
(up to 25°C; 77°F), after which the product
must be used or immediately discarded.
Do not use after the expiration date.
Do not freeze.
Grifols Therapeutics LLC
Research Triangle Park, NC 27709 USA
GRIFOLS
U.S. License No. 1871
3058828
Lot / Exp. / mg α1-PI